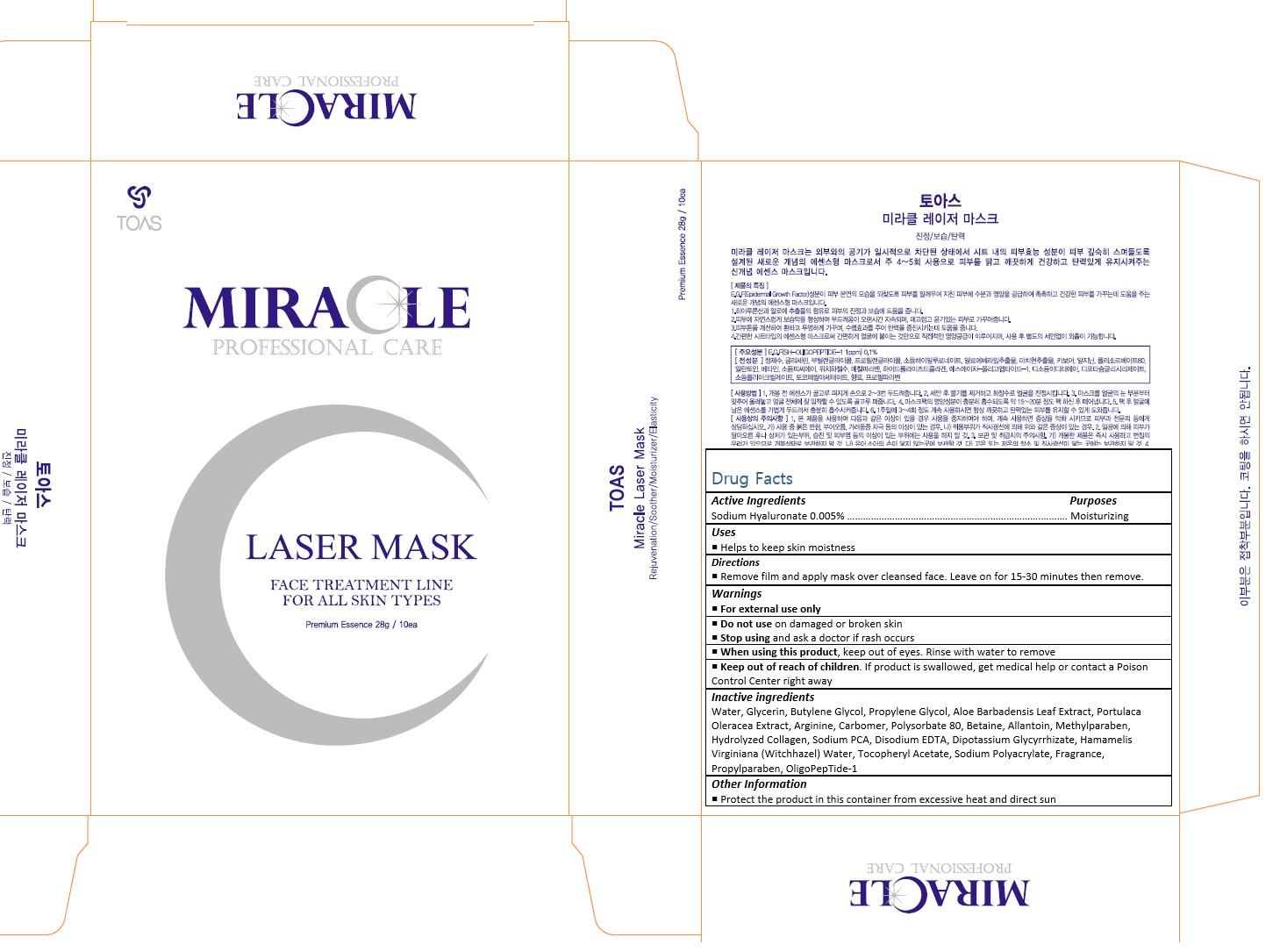 DRUG LABEL: Miracle Laser Mask
NDC: 72557-005 | Form: CREAM
Manufacturer: TOAS Co., Ltd.
Category: otc | Type: HUMAN OTC DRUG LABEL
Date: 20180924

ACTIVE INGREDIENTS: HYALURONATE SODIUM 0.0014 g/28 g
INACTIVE INGREDIENTS: WATER; GLYCERIN; BUTYLENE GLYCOL; PROPYLENE GLYCOL; ALOE VERA LEAF; ARGININE; CARBOXYPOLYMETHYLENE; POLYSORBATE 80; BETAINE; ALLANTOIN

72557-005_Miracle Laser Mask

ACTIVE INGREDIENT

Sodium Hyaluronate 0.005%

PURPOSE

Moisturizing

INDICATIONS AND USAGE

Helps to keep skin moistness

DOSAGE AND ADMINISTRATION

Remove film and apply mask over cleansed face. Leave on for 15-30 minutes then remove.

WARNINGS

For external use only.
Do not use on damaged or broken skin.
When using this product, keep out of eyes. Rinse with water to remove.
Stop using and ask a doctor if rash occurs.

KEEP OUT OF REACH OF CHILDREN

Keep out of reach of the children. If product is swallowed, get medical help or contact a poison control center right away.

INACTIVE INGREDIENT

Water, Glycerin, Butylene Glycol, Propylene Glycol, Aloe Barbadensis Leaf Extract, Portulaca Oleracea Extract, Arginine, Carbomer, Polysorbate 80, Betaine, Allantoin, Methylparaben, Hydrolyzed Collagen, Sodium PCA, Disodium EDTA, Dipotassium Glycyrrhizate, Hamamelis Virginiana (Witchhazel) Water, Tocopheryl Acetate, Sodium Polyacrylate, Fragrance, Propylparaben, OligoPepTide-1